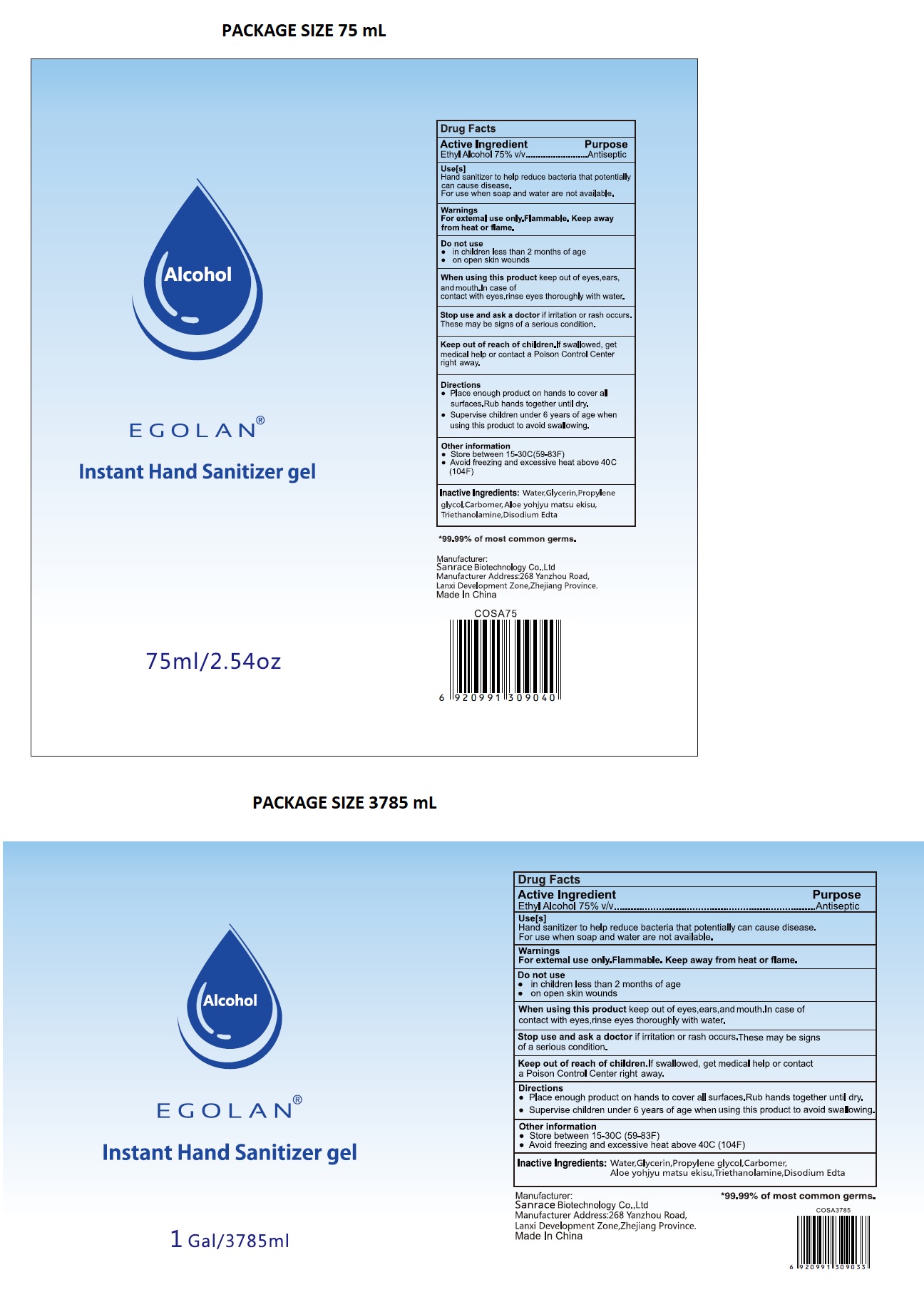 DRUG LABEL: EGOLAN Instant Hand Sanitizer gel
NDC: 75448-031 | Form: GEL
Manufacturer: Sanrace Biotechnology Co., Ltd.
Category: otc | Type: HUMAN OTC DRUG LABEL
Date: 20210104

ACTIVE INGREDIENTS: ALCOHOL 75 mL/100 mL
INACTIVE INGREDIENTS: WATER; GLYCERIN; PROPYLENE GLYCOL; CARBOMER HOMOPOLYMER, UNSPECIFIED TYPE; ALOE VERA LEAF; TROLAMINE; EDETATE DISODIUM ANHYDROUS

EGOLAN® Instant Hand Sanitizer gel

Active Ingredient

Ethyl Alcohol 75% v/v

Purpose

Antiseptic

Use[s]

Hand sanitizer to help reduce bacteria that potentially can cause disease.

For use when soap and water are not available.

Warnings

For external use only. Flammable. Keep away from heat or flame.

Do not use

• in children less than 2 months of age
• on open skin wounds

When using this product keep out of eyes, ears and mouth. In case of contact with eyes, rinse eyes thoroughly with water.

Stop use and ask a doctor if irritation or rash occurs. These may be signs of a serious condition.

Keep out of reach of children. If swallowed, get medical help or contact a Poison Control Center right away.

Directions

- Place enough product on hands to cover all surfaces. Rub hands together until dry.
- Supervise children under 6 years of age when using this product to avoid swallowing.

Other information

- Store between 15-30C (59-83F)
- Avoid freezing and excessive heat above 40C (104F)

Inactive Ingredients:

Water,Glycerin,Propylene glycol,Carbomer,Aloe yohjyu matsu ekisu,Triethanolamine,Disodium Edta

*99.99% of most common germs.

Manufacturer:

Sanrace Biotechnology Co.,Ltd

Manufacturer Address:268 Yanzhou Road,

Lanxi Development Zone,Zhejiang Province.

Made In China